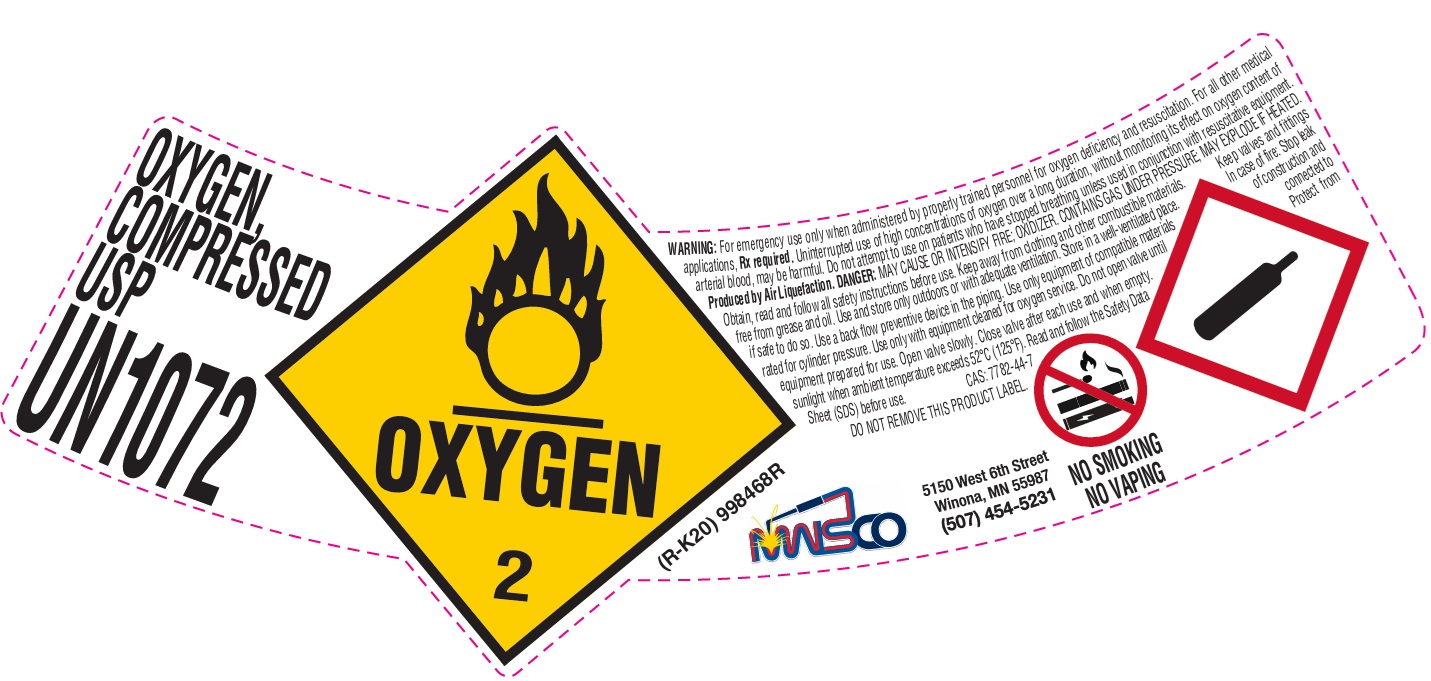 DRUG LABEL: Oxygen
NDC: 51996-011 | Form: GAS
Manufacturer: Mississippi Welders Supply Company, Inc.
Category: animal | Type: PRESCRIPTION ANIMAL DRUG LABEL
Date: 20251125

ACTIVE INGREDIENTS: Oxygen 990 mL/1 L

oxygen

PACKAGE LABEL

OXYGEN, COMPRESSED USP
UN1072
WARNING: For emergency use only when administered by properly trained personnel for oxygen deficiency and resuscitation. For all other medical applications, Rx required. Uninterrupted use of high concentrations of oxygen over a long duration, without monitoring its effect on oxygen content of arterial blood, may be harmful. Do not attempt to use on patients who have stopped breathing unless used in conjunction with resuscitative equipment. Produced by Air Liquefaction. DANGER: MAY CAUSE OR INTENSIFY FIRE; OXIDIZER. CONTAINS GAS UNDER PRESSURE; MAY EXPLODE IF HEATED. Obtain, read and follow all safety instructions before use. Keep away from clothing and other combustible materials. Keep valves and fittings free from grease and oil. Use and store only outdoors or with adequate ventilation. Store in a well-ventilated place. In case of fire: Stop leak if safe to do so. Use a back flow preventive device in the piping. Use only equipment of compatible materials of construction and rated for cylinder pressure. Use only with equipment cleaned for oxygen service. Do not open valve until connected to equipment prepared for use. Open valve slowly. Close valve after each use and when empty. Protect from sunlight when ambient temperature exceeds 52 C (125 F). Read and follow the Safety Data Sheet (SDS) before use. CAS: 7782-44-7 DO NOT REMOVE THIS PRODUCT LABEL.
MWSCO
5150 West 6th Street
Winona, MN 55987
(507) 454-5231
NO SMOKING
NO VAPING